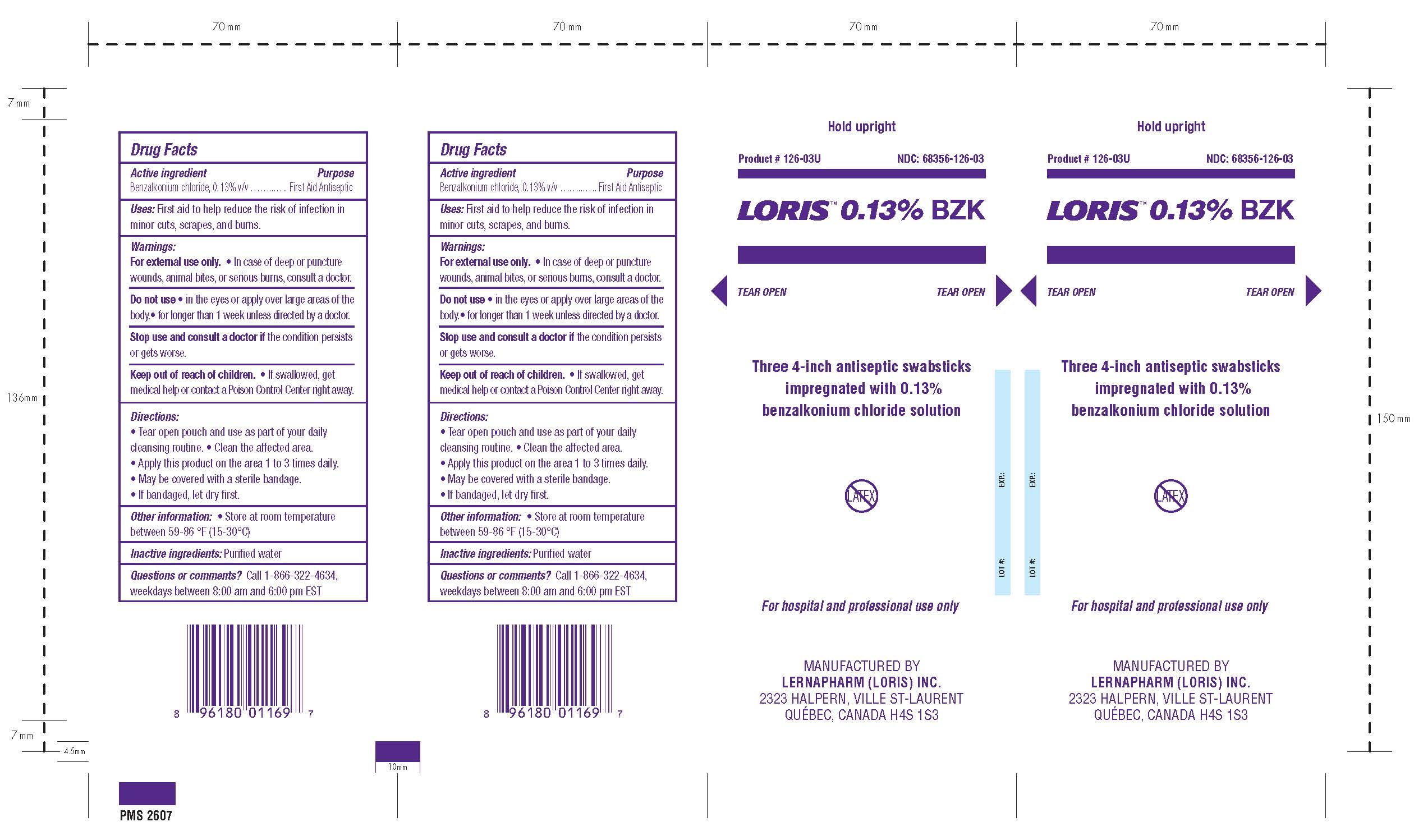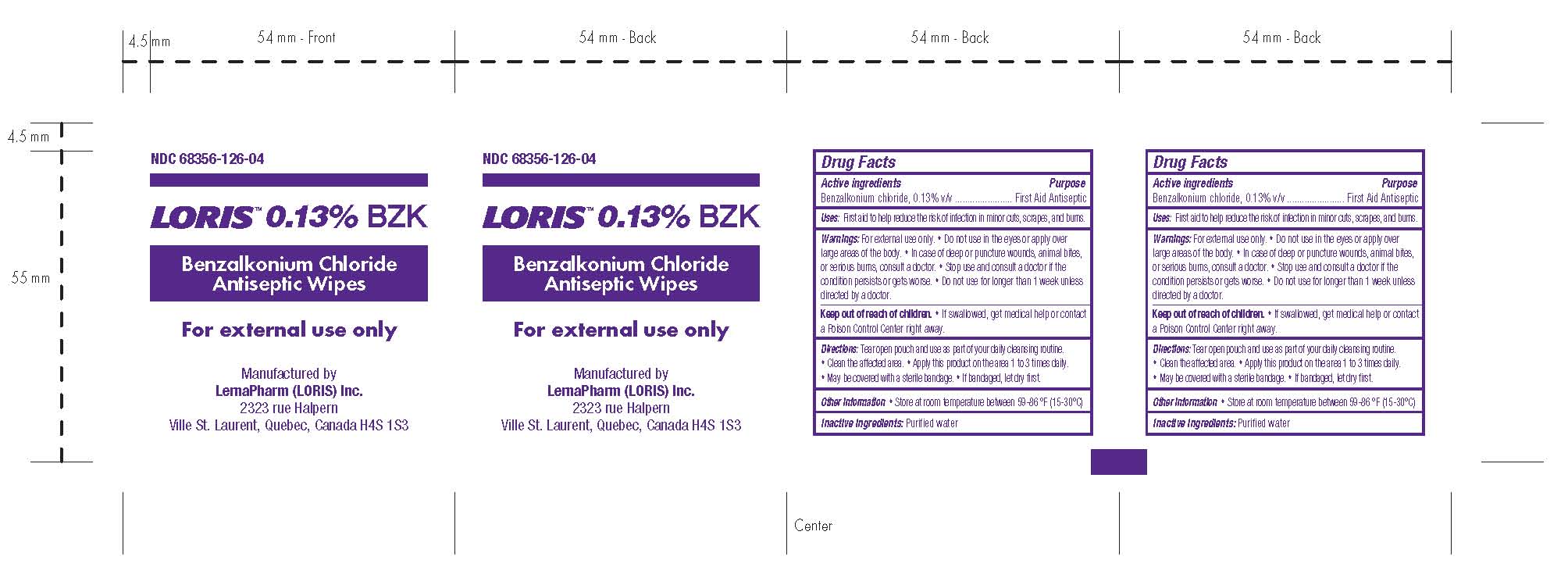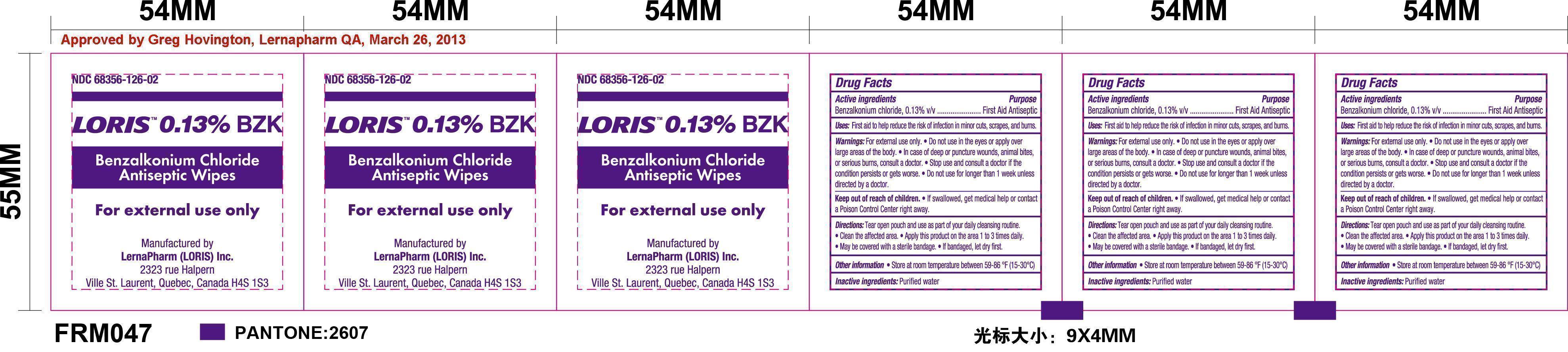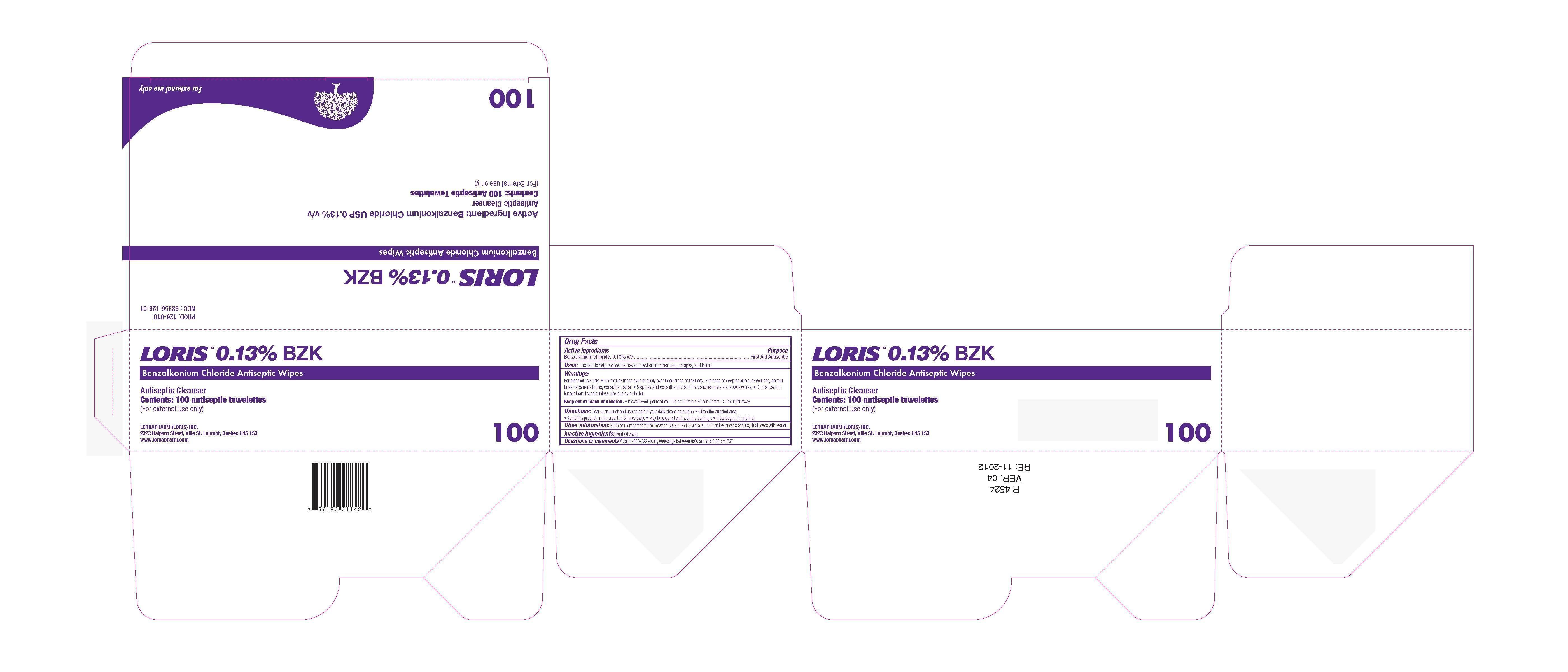 DRUG LABEL: Loris BZK
NDC: 68356-126 | Form: SWAB
Manufacturer: LernaPharm Loris Inc.
Category: otc | Type: HUMAN OTC DRUG LABEL
Date: 20230215

ACTIVE INGREDIENTS: BENZALKONIUM CHLORIDE 0.13 g/100 g
INACTIVE INGREDIENTS: WATER

Drug Facts

Active Ingredients

Benzalkonium chloride, 0.13% v/v

Purpose

First Aid Antiseptic

Uses

First aid to help reduce the risk of infection in minor cuts, scrapes, and burns.

Warnings

For External Use Only

- Do not use in the eyes or apply over large areas of the body.
- In case of deep or puncture wounds, animal bites, or serious burns, consult a doctor.
- Stop use and consult a doctor if the condition persists or gets worse.
- Do not use for longer than 1 week unless directed by a doctor.

Keep out of reach of children. If swallowed get medical help or contact a Poison Control Center right away.

Directions

- Tear open pouch and use as part of your daily cleansing routine.
- Clean the affected area.
- Apply this product on the area 1 to 3 times daily.
- May be covered with a sterile bandage.
- If bandaged, let dry first.

Other Information

Store at room temperature between 59-86oF (15-30oC). If contact with eyes occurs, flush eyes with water.

Inactive Ingredients

Purified water

Questions or comments?

Call 1-866-322-4634, weekdays between 8:00 am and 6:00 pm EST

PACKAGE LABEL

Place holder text